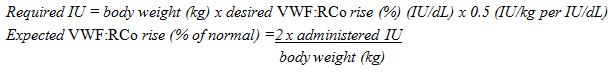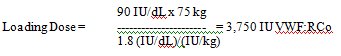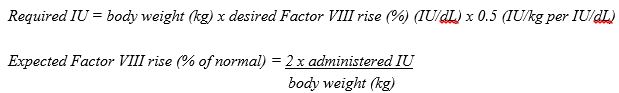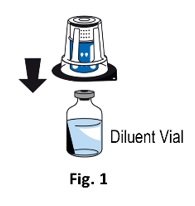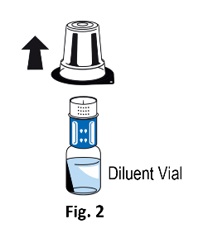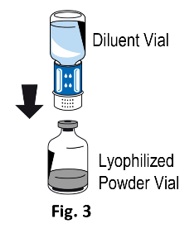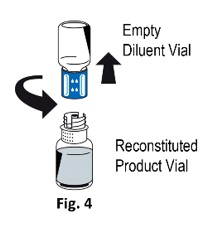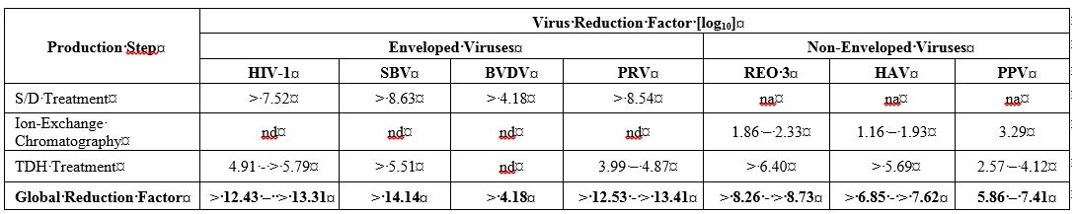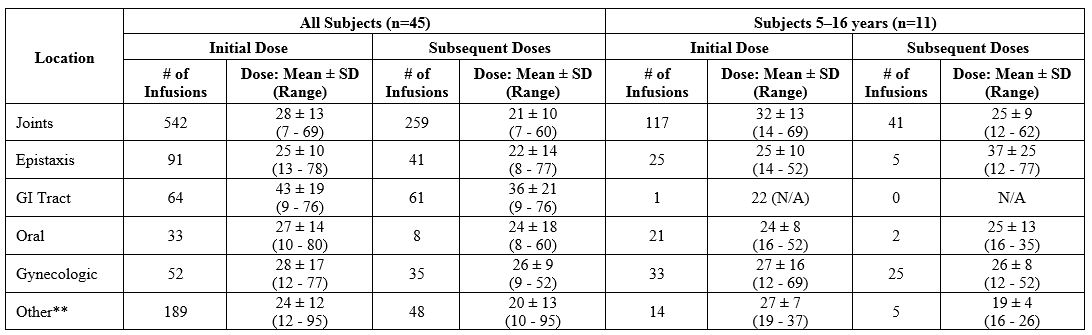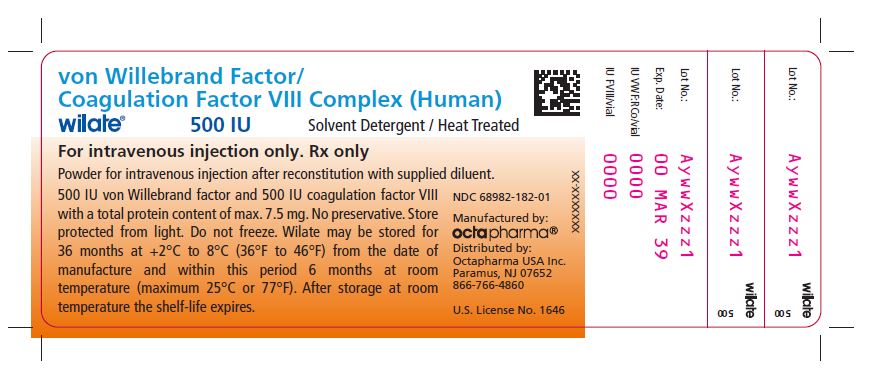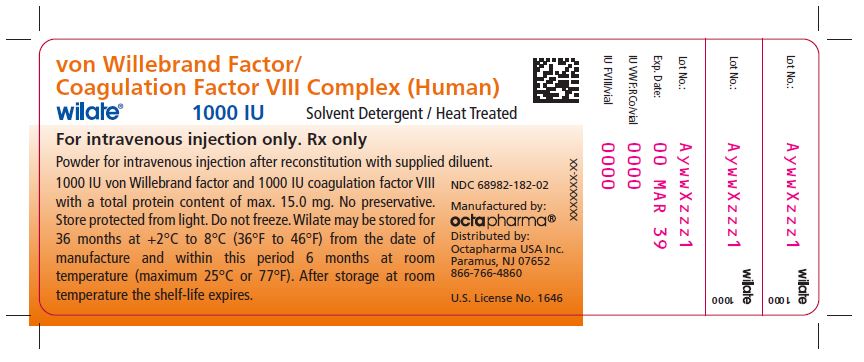 DRUG LABEL: Wilate - von Willebrand Factor/Coagulation Factor VIII Complex (Human)
NDC: 68982-182 | Form: POWDER, FOR SOLUTION
Manufacturer: Octapharma USA Inc
Category: other | Type: PLASMA DERIVATIVE
Date: 20241119

ACTIVE INGREDIENTS: ANTIHEMOPHILIC FACTOR HUMAN 100 [iU]/1 mL; VON WILLEBRAND FACTOR HUMAN 100 [iU]/1 mL

HIGHLIGHTS OF PRESCRIBING INFORMATION

These highlights do not include all the information needed to use WILATE safely and effectively. See full prescribing information for WILATE.
WILATE, von Willebrand Factor/Coagulation Factor VIII Complex (Human)
Lyophilized Powder for Solution for Intravenous Injection
Initial U.S. Approval: 2009
----------------------------RECENT MAJOR CHANGES-------------------
Indication and Usage (1) 12/2023
Dosage and Administration (2.2, 2.3) 11/2024

1 INDICATIONS AND USAGE

WILATE is indicated in children and adults with von Willebrand disease for:

On-demand treatment and control of bleeding episodes (1)

Perioperative management of bleeding (1)

Routine prophylaxis to reduce the frequency of bleeding episodes (1)

Wilate is indicated for routine prophylaxis in children 6 years of age and older and adults with von Willebrand disease.

WILATE is indicated in adolescents and adults with hemophilia A for:

Routine prophylaxis to reduce the frequency of bleeding episodes

On-demand treatment and control of bleeding episodes (1)

2 DOSAGE AND ADMINISTRATION

For Intravenous Use Only

Von Willebrand Disease

Use the following formula to determine required dosage (2.1):

Required IU = body weight (BW) in kg x desired VWF:RCo rise (%) (IU/dL) x 0.5 (IU/kg per IU/dL)

Adjust dosage and duration of the substitution therapy depending on the severity of the VWD, on the location and extent of the bleeding, and on the patient’s clinical condition (2.1)

The recommended infusion rate of 2-4ml/min

On-demand treatment and control of bleeding episodes

Dosing recommendations (2.1):

Type of Hemorrhages | Loading Dosage (IU VWF:RCo/ kg BW) | Maintenance Dosage (IU VWF:RCo/ kg BW) | Therapeutic Goal
Minor Hemorrhages | 20-40 IU/kg | 20-30 IU/kg every 12-24 hours | VWF:RCo and FVIII activity trough levels of >30%
Major Hemorrhages | 40-60 IU/kg | 20-40 IU/kg every 12-24 hours | VWF:RCo and FVIII activity trough levels of >50%

Perioperative management of bleeding

Dosing recommendations (2.1):

Type of Surgery | Loading Dosage (IU VWF:RCo/ kg BW) | Maintenance Dosage (IU VWF:RCo/ kg BW) | Therapeutic Goal
Minor Surgeries (including tooth extractions) | 30-60 IU/kg | 15-30 IU/kg or half the loading dose every 12-24 hours for up to 3 days | VWF:RCo peak level of 50% after loading dose and trough levels of > 30% during maintenance doses
Major Surgeries | 40-60 IU/kg | 20-40 IU/kg or half the loading dose every 12-24 hours for up to 6 days or more | VWF:RCo peak level of 100% after loading dose and trough levels of > 50% during maintenance doses

In order to decrease the risk of perioperative thrombosis, FVIII activity levels should not exceed 250%.

Routine prophylaxis to reduce the frequency of bleeding episodes

Dosing recommendations (2.1):

Patients | Dose (IU/kg) | Frequency of infusions
Age 6 and older | 20 – 40 IU/kg | Two or three times per week

Hemophilia A

One International Unit (IU) of factor VIII (FVIII) activity per kg body weight increases the circulating FVIII level by approximately 2 IU/dL (1.7 IU/dL for adolescents and 2.3 IU/dL for adults) (2.1).

Use the following formula to determine required dosage (2.1):

Required IU = body weight (BW) in kg x desired Factor VIII rise (%) (IU/dL) x 0.5 (IU/kg per IU/dL)

The recommended infusion rate of 2-4ml/min

Dosing for routine prophylaxis (2.1):

Patients | Dose (IU/kg) | Frequency of infusions
Adolescents and adults | 20-40 IU/kg | Every 2 to 3 days

Dosing for on-demand treatment and control of bleeding episodes (2.1)

Type of Hemorrhages | Recommended dosage (IU/kg body weight) | Frequency of Doses (hours) | Duration of Therapy (days)
Minor | 30-40 | Repeat every 12-24 hours | At least 1 day, until the hemorrhage has resolved
Moderate | 30-40 | Repeat every 12-24 hours | 3 to 4 days or more, until the hemorrhage has resolved
Major | 35-50 | Repeat every 12-24 hours | 3 to 4 days or more, until the hemorrhage has resolved
Life-threatening | 35-50 | Repeat every 8-24 hours | Until threat has resolved

Individualize dosage based on the patient’s weight, type and severity of hemorrhage, FVIII level, presence of inhibitors and the patient’s clinical condition (2.1).

3 DOSAGE FORMS AND STRENGTHS

WILATE is available as a sterile, lyophilized powder for reconstitution for intravenous injection, provided in the following nominal strengths per single-dose vial (3):

500 IU VWF:RCo and 500 IU FVIII activities in 5 mL

1000 IU VWF:RCo and 1000 IU FVIII activities in 10 mL

4 CONTRAINDICATIONS

Do not use in patients with known hypersensitivity reactions, including anaphylactic or severe systemic reaction, to human plasma-derived products, any ingredient in the formulation, or components of the container (4)

5 WARNINGS AND PRECAUTIONS

Anaphylaxis and severe hypersensitivity reactions are possible (5.1).

Thromboembolic events may occur. Monitor plasma levels of FVIII activity (5.2).

Development of neutralizing antibodies to FVIII and to VWF, especially in VWD type 3 patients, may occur (5.3).

WILATE is made from human plasma and carries the risk of transmitting infectious agents (5.4).

6 ADVERSE REACTIONS

The most common adverse reactions (≥ 1%) in clinical trails on VWD were hypersensitivity reactions, urticaria, chest discomfort, and dizziness (6.1)

The most common adverse reaction (≥ 1%) in clinical trails in hemophilia A was pyrexia (fever) (6.1).

To report SUSPECTED ADVERSE REACTIONS, contact Octapharma USA Inc. at 1-866-766-4860 or FDA at 1-800-FDA-1088 or www.fda.gov/medwatch.

Revised: November 2024

______________________________________________________________________________________________________________________________________

FULL PRESCRIBING INFORMATION

1 INDICATIONS AND USAGE

WILATE is indicated in children and adults with von Willebrand disease for:

- On-demand treatment and control of bleeding episodes
- Perioperative management of bleeding
- Routine prophylaxis to reduce the frequency of bleeding episodes

WILATE is indicated in adolescents and adults with hemophilia A for:

- Routine prophylaxis to reduce the frequency of bleeding episodes
- On-demand treatment and control of bleeding episodes

2 DOSAGE AND ADMINISTRATION

For Intravenous Use after Reconstitution

2.1 Dose

- Initiate treatment under the supervision of a physician experienced in the treatment of coagulation disorders.
- Each vial of WILATE contains the labeled amount in International Units (IU) of von Willebrand factor (VWF) activity as measured with the Ristocetin cofactor assay (VWF:RCo), and coagulation factor VIII (FVIII) activity measured with the chromogenic substrate assay.
- The number of units of VWF:RCo and FVIII activities administered is expressed in IU, which is related to the current WHO standards for VWF and FVIII products. VWF:RCo and FVIII activities in plasma are expressed either as a percentage (relative to normal human plasma) or in IU (relative to the International Standards for VWF:RCo and FVIII activities in plasma). One IU of VWF:RCo activity is equivalent to the quantity of VWF:RCo in one mL of normal human plasma. One IU of FVIII activity is defined by the quantity of Factor VIII in one mL of normal human pooled plasma. The ratio between VWF:RCo and FVIII activities in WILATE is approximately 1:1.

VWD

- Calculate the required dosage of VWF:RCo, based on the empirical finding that 1 IU VWF:RCo per kg body weight raises the plasma VWF activity by approximately 2% of normal activity or 2 IU/dL, using the following formula:

- Adjust the dosage and frequency of administration according to the clinical effectiveness in the individual patient.

Dosing for Hemorrhages

A guide for dosing in the treatment of major and minor hemorrhages is provided in Table 1 .

Table 1 Dosing for Treatment of Minor and Major Hemorrhages in all VWD types

Type of Hemorrhages | VWF:RCo and FVIII Activity Trough Levels (% of normal) | Loading Dosage (IU VWF:RCo/kg body weight) | Maintenance Dosage (IU VWF:RCo/kg body weight) | Frequency of Doses (hours) | Duration of Therapy (days)
Minor | >30 | 20-40 | 20-30 | Repeat as needed 12-24 | Up to 3 days
Major | >50 | 40-60 | 20-40 | Repeat as needed 12-24 | Up to 5-7 days

- Adjust the dose according to the extent and location of bleeding and the patient’s clinical condition. In VWD type 3 patients, those with gastro-intestinal (GI) bleedings may require higher doses.
- Repeat doses as needed based upon repeat monitoring of appropriate clinical and laboratory measures.
- Perform appropriate laboratory tests on the patient’s plasma at suitable intervals to assure that adequate VWF:RCo and FVIII activity levels have been reached and are maintained.

Dosing for Surgeries

A guide for dosing in minor and major surgeries is provided in Table 2 .

Table 2 Dosing for Treatment in Minor and Major Surgeries in all VWD Types

Type of Surgery | Loading Dosage (IU VWF:RCo/kg body weight) (within 3 hours before surgery) | VWF:RCo Peak Levels (% of normal) | Maintenance Dosage (IU VWF:RCo/kg body weight) | VWF:RCo Trough Levels (% of normal) | Frequency of Doses (hours) | Duration of Therapy (days)
Minor (including tooth extraction) | 30-60 | 50 | 15-30 or half the loading dose | >30 | 12-24 | Until wound healing achieved, up to 3 days
Major | 40-60 | 100 | 20-40 or half the loading dose | >50 | 12-24 (at least 2 doses within first 24 hours after the start of surgery) | Until wound healing achieved, up to 6 days or more

In order to decrease the risk of perioperative thrombosis, FVIII activity levels should not exceed 250%.

Whereas table 2 provides a dosing range that is expected to provide the desired peak levels of VWF:RCo, the following is an example on how to calculate the loading dose based on a patient’s individual IVR which is to be determined pre-surgery.

- Prior to surgery, measure incremental in vivo recovery (IVR) and assess baseline plasma VWF:RCo activity. The IVR for VWF:RCo provides the IU/dL rise per IU/kg body weight infused and can be measured and calculated as follows:
- Measure plasma VWF:RCo at baseline
- Infuse 60 IU VWF:RCo/kg of WILATE intravenously at time 0
- Measure plasma VWF:RCo at 30 minutes after the infusion

IVR = (Plasma VWF:RCo 30 min – Plasma VWF:RCo baseline)/60IU kg

- Calculation of the loading dose requires four values: the target peak plasma VWF:RCo level, the baseline VWF:RCo level, body weight (BW) in kilograms, and IVR. If the actual IVR calculation exceeds 2.5, use 2.5 to calculate the recommended loading dosing to avoid under-dosing. If IVR is not available, a standardized dose can be calculated based on an assumed VWF:RCo IVR of 2.0 U/dL per IU/kg of WILATE administered.

Example:

Assumption: Baseline VWF:RCo value = 10 IU/dL, and VWF:RCo target level = 100 IU/dL = Δ 90 IU/dL

Assumption: Patient’s weight = 75 kg, patient’s IVR = 1.8 (IU/dL)/(IU/kg)

When possible post surgery, perform appropriate laboratory tests on the patient’s plasma once a day after surgery to assure that adequate VWF:RCo and FVIII activity levels have been reached and are maintained. In order to decrease the risk of perioperative thrombosis, FVIII activity levels should not exceed 250%. [ 2 ]

Dosing for routine prophylactic treatment

A guide for dosing WILATE for routine prophylaxis to reduce the frequency of bleeding is provided in Table 3 . Exact dosing should be defined by the severity of VWD and by the patient’s clinical status and response.

Table 3 Dosing for Routine Prophylaxis

Patients | Dose (IU/kg) | Frequency of infusions
Age 6 and older | 20 – 40 IU/kg | Two or three times per week

Hemophilia A

- Calculation of the required dose of Factor VIII is based on the empirical finding that 1 IU Factor VIII per kg body weight raises the plasma Factor VIII activity by approximately 2% of normal activity or 2 IU/dL when assessed using the one stage clotting assay. Use the following formula to determine the required dose:

- Dose and duration of therapy depend on the patient’s weight, type and severity of hemorrhage, FVIII level, and presence of inhibitors.

Titrate dose and frequency to the patient’s clinical response, individual needs, severity of deficiency, severity of hemorrhage, desired FVIII level, and presence of inhibitor, and the patient’s clinical condition. Patients may vary in their pharmacokinetic (e.g., half-life, in vivo recovery) and clinical responses to WILATE.

Routine Prophylaxis

A guide for dosing WILATE for routine prophylaxis to reduce the frequency of bleeding is provided in Table 4 . Exact dosing should be defined by the patient’s clinical status and response.

Table 4 Dosing for Routine Prophylaxis

Patients | Recommended Dosage (IU/kg body weight) | Frequency of Infusions
Adolescents and adults | 20-40 IU/kg | Every 2 to 3 days

Dosing for Hemorrhages

A guide for dosing in the treatment of hemorrhages is provided in Table 5 .

Table 5 Dosing for Treatment of Hemorrhages

Type of Hemorrhages* | Recommended dosage (IU/kg body weight) | Frequency of Doses (hours) | Duration of Therapy (days)
Minor | 30-40 | Repeat every 12-24 hours | At least 1 day, until the hemorrhage has resolved
Moderate | 30-40 | Repeat every 12-24 hours | 3 to 4 days or more, until the hemorrhage has resolved
Major | 35-50 | Repeat every 12-24 hours | 3 to 4 days or more, until the hemorrhage has resolved
Life-threatening | 35-50 | Repeat every 8-24 hours | Until threat has resolved

*Minor hemorrhages may include e.g. early onset muscle and joint bleeds with no visible symptoms, such as little or no change in the range of motion of affected joint, mild restriction of mobility and activity, scrapes, superficial cuts, bruises, superficial mouth bleeds, and most nose bleeds; moderate hemorrhages may include e.g. advanced soft tissue and muscle bleeds into the limbs, bleeding into the joint space, such as the elbow, knee, ankle, wrist, shoulder, hip, foot, or finger; major hemorrhages may include e.g. complicated joint bleeds, bleeds of the pelvic muscles, eyes, and life-threatening hemorrhages may include e.g. bleedings in the abdomen, digestive system or chest, central nervous system bleeds, bleedings in the area of the neck or throat or pharynx, or other major trauma.

- Monitoring parameters
- Monitor plasma FVIII levels periodically to evaluate individual patient response to the dosage regimen.
- If dosing studies have determined that a particular patient exhibits a lower/higher than expected response and shorter/longer half-life, adjust the dose and the frequency of dosing accordingly
- Failure to achieve the expected FVIII:C level or to control bleeding after an appropriately calculated dosage may be indicative of the development of an inhibitor (an antibody to FVIII:C). Quantitate the inhibitor level by appropriate laboratory procedures and document its presence. Treatment with WILATE in such cases must be individualized.

2.2 Preparation and Reconstitution

- WILATE is provided with a Nextaro ® transfer device for reconstitution of the freeze-dried powder in diluent, a 10 mL syringe, an infusion set and two alcohol swabs.
- Reconstitute the powder only directly before injection. Because WILATE contains no preservatives, use the solution within 4 hours after reconstitution.

Instructions for Reconstitution:

1) Warm the powder (WILATE) and Diluent in the closed vials up to room temperature. If a water bath is used for warming, avoid water contact with the rubber stoppers or the caps of the vials. The temperature of the water bath should not exceed +37°C (98°F).
2) Remove the caps from the powder (WILATE) vial and the diluent vial and clean the rubber stoppers with an alcohol swab.

3) Open the transfer device package by peeling off the lid. To maintain sterility, leave the Nextaro ® device in the clear outer packaging. The transfer device must be attached to the diluent vial first and then to the lyophilized powder vial. Otherwise, loss of vacuum occurs, and transfer of the diluent does not take place. If diluent is not completely transferred to the lyophilized powder vial during this process, contact Octapharma’s customer service.
Place the diluent vial on a level surface and hold the vial firmly. Ensure the Nextaro ® device remains in the outer packaging and invert the Nextaro ® device ensuring the blue part with the water droplets is on top of the diluent vial. Push the Nextaro ® straight and firmly down until it snaps into place (Fig. 1). Do not twist while attaching. While holding onto the diluent vial, remove the outer package from the Nextaro ® , leaving the Nextaro ® attached firmly to the diluent vial (Fig. 2).

4) With the powder (WILATE) vial held firmly on a level surface, quickly invert the diluent vial with the Nextaro ® attached. Place the white part of the Nextaro ® on top of the powder (WILATE) vial until it snaps into the place (Fig. 3). Do not twist while attaching. The diluent will be drawn into the powder (WILATE) vial by the vacuum.
5)With both vials still attached, immediately start swirling the powder (WILATE) vial to ensure the powder is fully saturated. A slight whirlpool is formed by swirling. In order to avoid foaming, please do not shake the vial.

6) After 30 seconds, firmly hold both the white and blue parts of the Nextaro ® . Unscrew the Nextaro ® into two separate pieces (Fig. 4) and discard the empty diluent vial and the blue part of the Nextaro ® . Continue swirling until the powder in the WILATE vial has completely dissolved. This process may take several minutes.
The final solution is clear or slightly opalescent, colorless or slightly yellow. If the powder fails to dissolve completely or an aggregate is formed, do not use the preparation.

For intravenous injection after reconstitution only

1. Inspect final solution visually for particulate matter and discoloration prior to administration, whenever solution and container permit.
2. Do not mix WILATE with other medicinal products or administer simultaneously with other intravenous preparation in the same infusion set.
3. With the WILATE vial still upright, attach a plastic disposable syringe to the Nextaro ® (white plastic part). Invert the system and draw the reconstituted WILATE into the syringe.
4. Once WILATE has been transferred into the syringe, firmly hold the barrel of the syringe (keeping the syringe plunger facing down) and detach the Nextaro ® from the syringe. Discard the Nextaro ® (white plastic part) and empty WILATE vial.
5. Clean the intended injection site with an alcohol swab.
6. Attach a suitable infusion needle to the syringe.
7. Measure the patient’s pulse rate before and during the injection. If a marked increase in the pulse rate occurs, reduce the injection speed or interrupt the administration.
8. Inject the solution intravenously at a slow speed of 2-4 mL/minute.
9. Dispose unused product or waste material in accordance with local requirements.

3 DOSAGE FORMS AND STRENGTHS

WILATE is available as a sterile, lyophilized powder for reconstitution for intravenous injection, provided in the following nominal strengths per single-use vial:

- 500 IU VWF:RCo and 500 IU FVIII activities in 5 mL
- 1000 IU VWF:RCo and 1000 IU FVIII activities in 10 mL

4 CONTRAINDICATIONS

WILATE is contraindicated in patients with known hypersensitivity reactions, including anaphylactic or severe systemic reactions, to human plasma-derived products, any ingredient in the formulation [see Description (11) ] , or components of the container.

5 WARNINGS AND PRECAUTIONS

5.1 Hypersensitivity Reactions

Hypersensitivity reactions may occur with WILATE. Signs and symptoms include angioedema, burning and stinging at the infusion site, chills, flushing, generalized urticaria, headache, hives, hypotension, lethargy, nausea, restlessness, tachycardia, tightness of the chest, tingling, vomiting, and wheezing that may progress to severe anaphylaxis (including shock) with or without fever.[ 3 ] Closely monitor patients receiving WILATE and observe for any symptoms throughout the infusion period.

Because inhibitor antibodies may occur concomitantly with anaphylactic reactions, evaluate patients experiencing an anaphylactic reaction for the presence of inhibitors.[ 3 ] [see Warnings and Precautions (5.3)]

5.2 Thromboembolic Events

In VWD, continued treatment using a FVIII-containing VWF product may cause an excessive rise in FVIII activity [ 1 ], which may increase the risk of thromboembolic events. Monitor plasma levels of VWF:RCo and FVIII activities in patients receiving WILATE to avoid sustained excessive VWF and FVIII activity levels.

5.3 Neutralizing Antibodies

VWD

- Neutralizing antibodies (inhibitors) to FVIII and VWF in patients with VWD, especially type 3 patients, may occur. If a patient develops inhibitor to VWF (or to FVIII), the condition will manifest itself as an inadequate clinical response. Thus, if expected VWF activity plasma levels are not attained, or if bleeding is not controlled with an adequate dose or repeated dosing, perform an appropriate assay to determine whether a VWF inhibitor is present.
- In patients with antibodies against VWF, VWF is not effective and WILATE administration may lead to severe adverse events. Consider other therapeutic options for such patients.
- Because inhibitor antibodies may occur concomitantly with anaphylactic reactions, evaluate patients experiencing an anaphylactic reaction for the presence of inhibitors.[ 3 ] [see Warnings and Precautions (5.1)].

Hemophilia A

- Monitor plasma Factor VIII activity by performing a validated test (e.g., one stage clotting assay), to confirm that adequate Factor VIII levels have been achieved and maintained [see Dosage and Administration (2.1)] .
- Monitor for the development of Factor VIII inhibitors. Perform a Bethesda inhibitor assay if expected Factor VIII plasma levels are not attained, or if bleeding is not controlled with the expected dose of Wilate. Use Bethesda Units (BU) to report inhibitor levels.

5.4 Transmissible Infectious Agents

WILATE is made from human plasma. Because this product is made from human blood, it may carry a risk of transmitting infectious agents, e.g., viruses, and theoretically, the variant Creutzfeldt-Jakob disease (vCJD) agent. There is also the possibility that unknown infectious agents may be present in the product. The risk that WILATE will transmit viruses has been reduced by screening plasma donors for prior exposure to certain viruses, by testing for the presence of certain current virus infections, and by inactivating and removing certain viruses during manufacture. Despite these measures, it may still potentially transmit disease. [ 5 ]

Record the batch number of the product every time WILATE is administered to a patient, and consider appropriate vaccination (against hepatitis A and B virus) of patients in regular/repeated receipt of WILATE. ALL infections thought by a physician possibly to have been transmitted by this product should be reported by the physician or other healthcare provider to Octapharma USA, Inc., at 1-866-766-4860.

5.5 Monitoring and Laboratory Tests

- Monitor plasma levels of VWF:RCo and FVIII activities in patients receiving WILATE to avoid sustained excessive VWF and FVIII activity levels, which may increase the risk of thromboembolism, particularly in patients with known clinical or laboratory risk factors.
- Monitor for development of VWF and FVIII inhibitors. Perform assays to determine whether VWF and/or FVIII inhibitor(s) is present if bleeding is not controlled with the expected dose of WILATE. [ 6 ]

6 ADVERSE REACTIONS

The most common adverse reactions to treatment with WILATE (≥ 1%) in patients with VWD were hypersensitivity reactions, urticaria, chest discomfort, and dizziness. The most common adverse reactions to treatment with WILATE (≥ 1%) in previously treated patients with hemophilia A was pyrexia (fever).

Seroconversions for antibodies to parvovirus B19 not accompanied by clinical signs of disease have been observed.

The most serious adverse reactions to treatment with WILATE in patients with VWD and hemophilia A are hypersensitivity reactions [see Warnings and Precautions (5.1)].

6.1 Clinical Trials Experience

Because clinical trials are conducted under widely varying conditions, adverse reaction rates observed in the clinical trials of WILATE cannot be directly compared to rates in clinical trials of another drug and may not reflect the rates observed in clinical practice.

A total of 198 subjects treated for VWD (aged 1 to 83 years) received WILATE on 10761 occasions, including clinical studies that involved prophylactic use, treatment on demand, surgery, and pharmacokinetics. Of the 198 subjects, 37 (19%) had VWD type 1, 47 (23.7%) had VWD type 2, and 104 (52.5%) had VWD type 3 and 10 (5%) had an unknown status; 111 (56.1%) subjects were female and 87 (43.9%) subjects were male. Overall, subjects received 19;048;830 IU of WILATE during 10285 exposure days. The most common adverse drug reactions were hypersensitivity reactions (4 subjects; 2%), dizziness (3 subjects; 1.5%), urticaria and chest discomfort (each with 2 subjects; 1%).

A total of 136 hemophilia A previously treated subjects (aged 11 to 66 years) received WILATE in 5 clinical studies that involved prophylactic use, treatment on demand, surgery and/or pharmacokinetics. All subjects were male. Overall, subjects received 19,317,004 IU of WILATE during 9001 exposure days. The most common adverse reaction was pyrexia (2 subjects; 1.5%). Further adverse reactions included pruritus, headache and sleeping disorder (1 subject; 0.75%). Two out of 55 subjects (3.6%) in the pivotal study of routine prophylaxis in severe hemophilia A had unexplained transient worsening of pre-existing thrombocytosis while on the study.

Immunogenicity

The immunogenicity of WILATE in VWD was specifically assessed in 97 subjects in 3 clinical studies in which subjects received 9,635,041 IU of WILATE during 5575 exposure days. No inhibitors of VWF were detected in these 3 studies. In one of 3 studies, which also assessed FVIII inhibitor development in 15 subjects, no inhibitors of FVIII were detected after administration of a total of 223,290 IU of WILATE over 419 administrations.

The immunogenicity of WILATE in previously treated subjects with hemophilia A was specifically assessed in a pooled analysis that selected from 136 previously treated subjects included in 5 clinical studies those subjects who had at least 150 exposure days at the time of enrollment into the study and had been treated for at least 50 exposure days and 6 months in the study. Eighty three subjects fulfilled these criteria. None of them developed inhibitors to Factor VIII, resulting in a rate of inhibitor development of 0% (95% CI, 0-4.35%).

The detection of antibody formation is highly dependent on the sensitivity and specificity of the assay. Additionally, the observed incidence of antibody (including neutralizing antibody) positivity in an assay may be influenced by several factors including assay methodology, sample handling, timing of sample collection, concomitant medications, and underlying disease. For these reasons, comparison of the incidence of antibodies to WILATE with the incidence of antibodies to other products may be misleading.

6.2 Postmarketing Experience

The following adverse reactions have been identified during the post-approval use of WILATE. Because these reactions are reported voluntarily from a population of uncertain size, it is not always possible to reliably estimate their frequency or establish a causal relationship to product exposure.

Post-marketing adverse reactions including dyspnea, hypertension, cough, chest discomfort, abdominal pain, and back pain have been reported in patients treated with WILATE.

8 USE IN SPECIFIC POPULATIONS

8.1 Pregnancy

Risk Summary

There are no data with WILATE use in pregnant women to inform a drug-associated risk. Animal reproduction studies have not been conducted with WILATE. WILATE was given to four subjects (3 type 3 and 1 type 2B) during labor and delivery in one clinical study. Two subjects underwent vaginal delivery (type 3) and two subjects had a cesarean section (type 3/type 2B). In this study all procedures were uneventful.

In the U.S. general population, regardless of drug exposure, the estimated background risk of major birth defect and miscarriage in clinically recognized pregnancies is 2-4% and 15-20%, respectively.

8.2 Lactation

Risk summary

There is no information regarding the presence of WILATE in human milk, the effect on the breastfed infant, and the effects on milk production. The developmental and health benefits of breastfeeding should be considered along with the mother’s clinical need for WILATE and any potential adverse effects on the breastfed infant from WILATE or from the underlying maternal condition.

8.4 Pediatric Use

The safety and effectiveness of WILATE have been established for pediatric patients ≤16 years of age with vWD for the treatment and control of bleeding episodes and perioperative management. Eleven pediatric subjects with VWD between 5 to 16 years of age (8 type 3, 1 type 2, 2 type 1) were treated with WILATE for 234 bleeding episodes (BEs) in clinical studies. Treatment success was achieved in 88% of BEs [see Clinical Studies (14)] . Efficacy data during surgical prophylaxis were available for 13 pediatric VWD surgery subjects (3 subjects aged 0 to 2 years, 4 subjects aged 2 to 5 years, 3 subjects aged 6 to 12 years, and 3 subjects aged 12 to 16 years). Treatment success was achieved in 22 of 22 surgical procedures (17 minor and 5 major).

Efficacy of routine prophylaxis was investigated in 15 pediatric subjects between 6 and 16 years of age (9 type 3, 3 type 2 and 3 type 1). Total annualized bleeding rate decreased from 32.59 during on-demand treatment to 3.73 during routine prophylaxis with WILATE in the 9 subjects 6 to less than 12 years of age and from 28.99 to 4.28 in the 6 subjects 12 to less than 17 years of age.

The safety and effectiveness of WILATE have been established for pediatric patients ≥12 years of age with hemophilia A for the treatment and control of bleeding episodes and routine prophylaxis use. Five adolescents with hemophilia A between 12 und 15 years of age were treated with WILATE for routine prophylaxis in one clinical study. The annualized bleeding rate was mean 0.4 (standard deviation 0.9), median 0 (range 0-2). During 6 months of prophylaxis, one patient experienced one traumatic BE, which was treated successfully with WILATE. No dose adjustment is needed for pediatric patients ≥12 years of age as administered dosages were similar to those used in the adult population [see Clinical Studies (14)].

The safety and effectiveness of WILATE have not been established for pediatric patients <12 years of age with hemophilia A. In a clinical study that evaluated the pharmacokinetics of WILATE in 10 pediatric patients (2 to 11 years of age) with hemophilia A, effects on annualized bleeding rate were inconclusive.

8.5 Geriatric Use

Although some of the subjects who participated in the WILATE studies were over 65 years of age, the number of subjects was inadequate to allow subgroup analysis to support recommendations in the geriatric population.

11 DESCRIPTION

WILATE is a human plasma-derived, sterile, purified, double virus inactivated von Willebrand Factor/Coagulation Factor VIII Complex. WILATE is supplied as a lyophilized powder for reconstitution for intravenous injection. The diluent for reconstitution of the lyophilized powder is Water for Injection with 0.1% Polysorbate 80.

WILATE contains no preservative. No albumin is added as a stabilizer. WILATE is labeled with the actual VWF:RCo and FVIII activities in IU per vial. The VWF activity (VWF:RCo) is determined using a manual agglutination method referenced to the current “WHO International Standard for von Willebrand Factor Concentrate”. The FVIII activity is determined using a chromogenic substrate assay referenced to the current “WHO International Standard for Human Coagulation Factor VIII Concentrate”. The assay methodologies are according to European Pharmacopoeia (Ph.Eur.). The resulting specific activity of WILATE is ≥ 60 IU VWF:RCo and ≥ 60 IU FVIII activities per mg of total protein.

The nominal composition of WILATE is as follows:

Component | Quantity/ 5 mL vial | Quantity/ 10 mL vial
VWF:Rco | 500 IU | 1000 IU
FVIII | 500 IU | 1000 IU
Total protein | ≤ 7.5 mg | ≤ 15.0 mg
Glycine | 50 mg | 100 mg
Sucrose | 50 mg | 100 mg
Sodium chloride | 117 mg | 234 mg
Sodium citrate | 14.7 mg | 29.4 mg
Calcium chloride | 0.8 mg | 1.5 mg
Water for injection | 5 mL | 10 mL
Polysorbate 80 | 1 mg/mL | 1 mg/mL

Von Willebrand Factor/Coagulation Factor VIII complex is the active ingredient in WILATE. It is derived from large pools of human plasma collected in U.S. plasma donation centers. All plasma donations are tested for viral markers in compliance with requirements of EU CPMP and FDA guidance. In addition, the limit for the titer of human parvovirus B19 DNA in the manufacturing pool is set not to exceed 10 ^4 IU/mL.

The product is manufactured from cryoprecipitate, which is reconstituted in a buffer and treated with aluminum hydroxide followed by two different chromatography steps, ultra- and diafiltration, and sterile filtration. The manufacturing process includes two virus inactivation steps, namely, treatment with an organic solvent/detergent (S/D) mixture, composed of tri-n-butyl phosphate (TNBP) and Octoxynol-9, and a terminal dry heat (TDH) treatment of the lyophilized product in final container [at +100°C (212°F) for 120 minutes at a specified residual moisture level of 0.7-1.6%]. In addition, the ion-exchange chromatography step utilized during WILATE manufacturing also removes some viruses [ 8 ]. The mean cumulative virus reduction factors of these steps are summarized in Table 6 .

Table 6 Virus Reduction During WILATE Manufacturing

na: not applicable

nd: not done (S/D reagents present)

HIV-1: Human Immunodeficiency Virus - 1

SBV: Sindbis Virus

BVDV: Bovine Viral Diarrhea Virus

PRV: Pseudorabies Virus

REO 3: Reovirus Type 3

HAV: Hepatitis A Virus

PPV: Porcine Parvovirus

12 CLINICAL PHARMACOLOGY

12.1 Mechanism of Action

WILATE contains von Willebrand factor (VWF) and coagulation factor VIII (FVIII), constituents of normal plasma. VWF promotes platelet aggregation and platelet adhesion on damaged vascular endothelium; it also serves as a stabilizing carrier protein for the procoagulant protein FVIII, an essential cofactor in activation of factor X leading to formation of thrombin and fibrin. Patients suffering from VWD have a deficiency or abnormality of VWF. This reduction in VWF plasma concentration results in correspondingly low FVIII activity and abnormal platelet function, thereby resulting in excessive bleeding. [ 9 ] After administration, WILATE temporarily replaces missing VWF and FVIII that are needed for effective hemostasis. When infused into a patient with hemophilia A, FVIII binds to VWF in the patient´s circulation. Activated FVIII (FVIIIa) acts as a cofactor for activated factor IX (FIXa), accelerating the conversion of factor X to activated factor X (FXa). FXa converts prothrombin into thrombin. Thrombin then converts fibrinogen into fibrin and a clot can be formed. Hemophilia A is a sex-linked hereditary disorder of blood coagulation due to decreased levels of FVIII:C and results in profuse bleeding into joints, muscles or internal organs, either spontaneously or as a result of accidental or surgical trauma. By replacement therapy the plasma levels of FVIII are increased, thereby enabling a temporary correction of the factor deficiency and correction of the bleeding tendencies.

12.2 Pharmacodynamics

There have been no specific pharmacodynamic studies on WILATE.

12.3 Pharmacokinetics

VWD

Pharmacokinetic (PK) profiles of WILATE were determined by FVIII activity, VWF:RCo, VWF:Ag, and VWF:CB obtained from an open label, prospective, randomized, controlled, two-arm cross-over study with WILATE and a comparator product conducted at 6 sites in the US. Twenty-two subjects (≥ 12 years of age) with inherited VWD [type 1, n=6; type 2, n=9 (6 type 2A, 1 type 2B, and 2 type 2M); and type 3, n=7] received an intravenous bolus dose of WILATE containing approximately 40 IU of VWF:RCo/kg body weight. Twenty subjects completed the study as per protocol. PK parameters for VWF:RCo and FVIII activities are summarized in Table 7 and Table 8 , respectively. PK parameters for pediatric subjects are summarized in Table 9 , Table 10 , Table 11 , and Table 12 .

The PK parameters reported in Table 7 are based on VWF:RCo values obtained using a modified Behring Coagulation System (BCS) analytical method. The modified BCS was used because of its validated lower variability compared with the standard BCS. Measured concentrations (IU VWF:RCo/mL) are higher by the modified BCS than by the standard BCS analytical method which is used in some clinical laboratories. Dose adjusted C max and AUC determined by this modified BCS method are approximately 1.5 times higher than those by the standard BCS method. No difference has been found in incremental recovery.

The PK parameters reported in Table 9 , Table 10 , Table 11 , and Table 12 are based on values obtained from an open label, prospective, non-controlled, international, multi-center study in which a subset of pediatric subjects aged 6-16 years with inherited VWD underwent pharmacokinetic investigations before the start of prophylaxis treatment. Thirteen subjects [type 1, n=3; type 2, n=3, and type 3, n=7]) received an intravenous bolus dose of WILATE containing approximately 60 IU of VWF:RCo/kg body weight. Eight subjects were 6-11 years old and 5 subjects 12-16 years.

Table 7 Pharmacokinetic Parameters of VWF:RCo:mean ± SD (range)

Parameters | VWD type I (n = 5) | VWD type II (n = 9) | VWD type III (n = 6) | Total (n = 20)
C max (IU/dL) | 74 ± 13 (62 - 91) | 77 ± 18 (40 - 100) | 79 ± 13 (65 - 102) | 76 ± 15 (40 - 102)
AUC (0-inf) (IU*hr/dL) | 1633 ± 979 (984 - 3363) | 1172 ± 421 (571 - 1897) | 995 ± 292 (527 - 1306) | 1235 ± 637 (527 - 3363)
Half-life (hrs) | 24.7 ± 17.9 (11.2 - 48.5) | 15.3 ± 6.3 (6.0 - 26.4) | 9.1± 2.6 (5.7 - 12.9) | 15.8 ± 11.0 (5.7 - 48.5)
CL (mL/h/kg) | 3.1 ± 1.1 (1.2 - 4.1) | 4.1 ± 1.7 (2.0 - 7.1) | 4.2 ± 1.4 (3.0 - 6.6) | 3.9 ± 1.5 (1.2 - 7.1)
Vd (mL/kg) | 81.7 ± 38.5 (15.3 - 74.2) | 76.6 ± 35.4 (45.3 - 158.8) | 49.4 ± 16.7 (29.7 - 67.1) | 69.7 ± 33.2 (29.7 - 158.8)
MRT (hrs) | 32.7 ± 25.8 (15.3 - 74.2) | 19.7 ± 5.6 (9.9 - 27.1) | 11.9 ± 2.9 (9.2 - 15.9) | 20.6 ± 14.8 (9.2 - 74.2)
Recovery (%IU/kg) | 1.8 ± 0.2 (1.5 - 2.0) | 1.8 ± 0.5 (1.0 - 2.4) | 2.1 ± 0.3 (1.8 - 2.6) | 1.9 ± 0.4 (1.0 - 2.6)

C max = peak concentration; AUC = area under curve; CL = clearance; Vd= volume of distribution at steady state; MRT = mean residence time

Table 8 Pharmacokinetic Parameters of FVIII activity (chromogenic assay): mean ± SD (range)

Parameters | VWD type I (n = 5) | VWD type II (n = 8*) | VWD type III (n = 6) | Total (n = 19*)
C max (IU/dL) | 117.1 ± 12.1 (103 - 135) | 147.2 ± 32.6 (102 - 206) | 120 ± 23 (91 - 148) | 112 ± 23 (59 - 148)
AUC (0-inf) (IU*hr/dL) | 1187 ± 382 (523 - 1483) | 1778 ± 1430 (544 - 4821) | 2670 ± 854 (1874 - 3655) | 2290 ± 1045 (464 - 4424)
Half-life (hrs) | 17.5 ± 4.9 (10.9 - 23.8) | 23.6 ± 8.3 (12.6 - 34.7) | 16.1 ± 3.1 (11.8 - 20.1) | 19.6 ± 6.9 (10.9 - 34.7)
CL (mL/h/kg) | 4.4 ± 3.7 (2.5 - 11.0) | 2.5 ± 0.9 (1.2 - 3.5) | 2.0 ± 0.6 (1.4 - 2.8) | 2.9 ± 2.1 (1.2 - 11.0)
Vd (mL/kg) | 95.0 ± 53.8 (57.1 - 190.0) | 79.5 ± 23.1 (52.8 - 116.2) | 44.2 ± 10.4 (31.8 - 57.1) | 72.4 ± 36.2 (31.8 - 190.0)
MRT (hrs) | 24.1 ± 5.5(17.2 - 31.5) | 35.1 ± 14.2 (17.5 - 61.6) | 23.0 ± 3.7 (18.0 - 27.7) | 28.4 ± 11.1 (17.2 - 61.6)
Recovery (%IU/kg) | 1.9 ± 0.5 (1.1 - 2.5) | 2.2 ± 0.4 (1.6 - 2.8) | 2.5 ± 0.5 (2.0 - 3.0) | 2.2 ± 0.5 (1.1 - 3.0)

*One subject with implausible long half-life is not included in the summary table, except for recovery result.

C max = peak concentration; AUC = area under curve; CL = clearance; Vd = volume of distribution at steady state; MRT = mean residence time

Table 9 Pharmacokinetic Parameters of VWF:RCo in children 6-16 years per VWD type: mean ± SD (range)

Parameters | VWD type I (n = 3) | VWD type II (n = 3) | VWD type III (n = 7) | Total (n = 13)
C max (IU/dL) | 91.3 ± 1.3 (78.5 – 119.3) | 63.5 ± 1.5 (39.0 – 84.4) | 77.4 ± 1.1 (59.1 – 90.6) | 76.8 ± 1.3 (39.0 – 119.3)
AUC (0-inf) (IU*hr/dL) | 963 ± 1.0 (920 – 1003) | 1421 ± 2.2 (634 – 3084) | 822 ± 1.2 (657 – 1189) | 968 ± 1.5 (634 – 3084)
Half-life (hrs) | 6.9 ± 1.1 (6.5 – 7.4) | 17.4 ± 2.0 (8.6 – 32.5) | 6.5 ± 1.2 (4.9 – 8.5) | 8.3 ± 1.7 (4.9 – 32.5)
CL (dL/h/kg) | 0.1 ± 1.0 (0.1 – 0.1) | 0.0 ± 2.2 (0.0 – 0.1) | 0.1 ± 1.2 (0.1 – 0.1) | 0.1 ± 1.5 (0.0 – 0.1)
Vd (dL/kg) | 0.7 ± 1.2 (0.6 – 0.8) | 1.4 ± 1.9 (0.9 – 3.0) | 0.8 ± 1.2 (0.7 – 1.0) | 0.8 ± 1.5 (0.6 – 3.0)
MRT (hrs) | 10.8 ± 1.1 (9.6 – 12.3) | 32.8 ± 1.4 (24.4 – 46.3) | 10.4 ± 1.2 (8.0 – 13.1) | 13.7 ± 1.7 (8.0 – 46.3)
Recovery (%IU/kg) | 1.5 ± 1.3 (1.3 – 2.0) | 1.1 ± 1.5 (0.7 – 1.4) | 1.3 ± 1.2 (1.0 – 1.5) | 1.3 ± 1.3 (0.7 – 2.0)

C max = peak concentration; AUC = area under curve; CL = clearance; Vd = volume of distribution at steady state; MRT = mean residence time

Table 10 Pharmacokinetic Parameters of VWF:RCo in children 6-16 years per age class: mean ± SD (range)

Parameters | Age 6-11 years (n = 8) | Age 12-16 years (n = 5)
C max (IU/dL) | 73.0 ± 1.4 (39.0 – 119.3) | 83.2 ± 1.1 (77.7 – 90.6)
AUC (0-inf) (IU*hr/dL) | 945 ± 1.7 (634 – 3084) | 1005 ± 1.3 (714 – 1467)
Half-life (hrs) | 8.4 ± 1.8 (5.0 – 32.5) | 8.1 ± 1.6 (6.0 - 19.0)
CL (dL/h/kg) | 0.1 ± 1.7 – 0.1) | 0.1 ± 1.3 (0.0 – 0.1)
Vd (dL/kg) | 0.9 ± 1.7 (0.6 – 3.0) | 0.8 ± 1.2 (0.7 – 1.0)
MRT (hrs) | 14.2 ± 1.9 (8.0 – 46.3) | 13.0 ± 1.5 (10.2 – 24.4)
Recovery (%IU/kg) | 1.2 ± 1.4 (0.7 – 2.0) | 1.4 ± 1.1 (1.3 – 1.5)

C max = peak concentration; AUC = area under curve; CL = clearance; Vd = volume of distribution at steady state; MRT = mean residence time

Table 11 Pharmacokinetic Parameters of FVIII activity (chromogenic assay) in children 6-16 years per VWD type: mean ± SD (range)

Parameters | VWD type I (n = 3) | VWD type II (n = 3) | VWD type III (n = 7) | Total (n = 13)
C max (IU/dL) | 101.8 ± 1.0 (98.1 – 106.9) | 71.7 ± 1.4 (47.9 – 96.8) | 94.9 ± 1.2 (77.0 – 115.3) | 90.4 ± 1.3 (47.9 – 115.3)
AUC (0-inf) (IU*hr/dL) | 1760 ± 1.8 (923 – 2865) | 1377 ± 1.5 (883 – 2006) | 2335 ± 1.4 (1522 – 3599) | 1937 ± 1.5 (883 – 3599)
Half-life (hrs) | 14.1 ± 1.4 (10.0 – 18.7) | 19.3 ± 1.8 (9.8 – 30.1) | 13.5 ± 1.5 (6.4 – 21.8) | 14.8 ± 1.5 (6.4 – 30.1)
CL (dL/h/kg) | 0.0 ± 1.8 (0.0 – 0.1) | 0.0 ± 1.5 (0.0 – 0.1) | 0.0 ± 1.4 (0.0 – 0.0) | 0.0 ± 1.5 (0.0 – 0.1)
Vd (dL/kg) | 0.7 ± 1.2 (0.6 – 0.8) | 1.6 ± 1.6 (1.1 – 2.6) | 0.6 ± 1.2 (0.4 – 0.8) | 0.8 ± 1.6 (0.4 – 2.6)
MRT (hrs) | 19.9 ± 1.5 (12.3 – 27.6) | 35.8 ± 1.1 (33.4 – 38.4) | 23.8 ± 1.2 (18.1 – 31.9) | 25.1 ± 1.4 (12.3 – 38.4)

C max = peak concentration; AUC = area under curve; CL = clearance; Vd = volume of distribution at steady state; MRT = mean residence time

Table 12 Pharmacokinetic Parameters of Factor VIII activity (chromogenic assay) in children 6-16 years per age class: mean ± SD (range)

Parameters | Age 6-11 years (n = 8) | Age 12-16 years (n = 5)
C max (IU/dL) | 82.7 ± 1.3 (47.9 – 100.5) | 104.3 ± 1.1 (96.8 – 115.3)
AUC (0-inf) (IU*hr/dL) | 1607.3 ± 1.5 (882.6 – 3087.6) | 2609.3 ± 1.3 (2005.5 – 3599.3)
Half-life (hrs) | 12.2 ± 1.5 (6.4 – 24.3) | 20.3 ± 1.3 (15.4 – 30.1)
CL (dL/h/kg) | 0.04 ± 1.5 0.02 – 0.1) | 0.02 ± 1.3 (0.02 – 0.03)
Vd (dL/kg) | 0.9 ± 1.7 (0.4 – 2.6) | 0.7 ± 1.3 (0.5 – 1.1)
MRT (hrs) | 22.9 ± 1.4 (12.3 – 38.4) | 28.9 ± 1.2 (23.9 – 35.8)

C max = peak concentration; AUC = area under curve; CL = clearance; Vd = volume of distribution at steady state; MRT = mean residence

Hemophilia A

The pharmacokinetics (PK) of WILATE were evaluated in 21 (16 adults, and 5 adolescents aged 12-15 years) previously treated patients (PTPs) with severe Hemophilia A within a prospective, open-label, multicenter clinical study. The PK parameters (Table 13) were based on plasma Factor VIII activity measured by the one-stage clotting assay after a single intravenous infusion of a 50 IU/kg dose.

The PK profile obtained after 6 months of repeated dosing in adults and adolescents was comparable with the PK profile obtained after the first dose.

Table 13 Pharmacokinetic Parameters of WILATE in 21 Previously Treated Patients (PTP: Mean ± SD)

PK Parameters | Adults (n=16) | Adolescents (n=5)
C max (IU/dL) | 113.82 ± 20.53 (77.43 - 142.00) | 83.92 ± 9.40 (77.93 – 100.27)
AUC (IU*hr/dL) | 1562.10 ± 451.43 (721.92 - 2271.48) | 1009.74 ± 172.26 (816.23 - 1287.76)
AUC norm (IU*hr/dL) | 31.24 ± 9.03 (14.44 - 45.43) | 20.20 ± 3.45 (16.32 - 25.76)
Half-life (hrs) | 10.64 ± 2.69 (6.30 - 15.43) | 11.41 ± 1.93 (9.37 – 14.57)
CL (dL/h/kg) | 0.035 ± 0.013 (0.02 - 0.07) | 0.051 ± 0.008 (0.04 - 0.06)
Vd (dL/kg) | 0.53 ± 0.13 (0.36 - 0.82) | 0.73 ± 0.13 (0.53 - 0.85)
MRT (hrs) | 15.81 ± 3.63 (10.80 - 22.23) | 14.39 ± 1.83 (12.85 – 17.30)
Recovery (%IU/kg) | 2.27 ± 0.41 (1.54 - 2.83) | 1.66 ± 0.17 (1.55 – 1.95)

C max = peak concentration; AUC = area under curve; CL = clearance; Vd = volume of distribution at steady state; MRT = mean residence time

14 CLINICAL STUDIES

VWD

Treatment of Bleeding Episodes

Clinical efficacy of WILATE in the control of bleeding in subjects with VWD was determined in four prospective, open-label, non-controlled clinical studies (excluding PK study). For inclusion in the studies, subjects had to have inherited VWD (any type) that did not respond to desmopressin acetate. Subjects aged ≥12 to ≤65 years were eligible to enter three of the four studies, and subjects aged ≥6 to ≤85 years were eligible for one study. Exclusion criteria included the administration of other plasma-derived or blood products or desmopressin acetate 15 days before study entry, administration of acetylsalicylic acid 7 days before study entry, symptomatic infection, past or present inhibitor activity (3 studies), and severe liver or kidney disease (3 studies). A total of 70 VWD subjects with a mean age of 37 years (range 5–77 years) were enrolled in the studies, of whom 37 were type 3 and 30 were male. The total number of exposure days to WILATE for all investigations across the four studies ranged from 202 to 4917 days. Treated BEs were analyzed for efficacy using a set of objective criteria in addition to a subjective 4-point hemostatic efficacy scale (excellent, good, moderate and none) which was determined at the discretion of the investigator. In assessing efficacy using the objective criteria, treatment of a bleeding episode was classified as a success when none of the criteria listed below were met:

- the episode was additionally treated with another VWF-containing product (excluding whole blood)
- the subject received a blood transfusion during the episode
- follow-up treatment with a daily dosage of WILATE that was greater than or equal to 50% (≥ 50%) above the initial dose (for bleeding episodes with more than 1 day of treatment)
- treatment duration of more than 4 days (> 4 days) in cases of severe bleeding (other than gastrointestinal)
- treatment duration of more than 3 days (> 3 days) in cases of moderate bleeding (other than gastrointestinal)
- treatment duration of more than 2 days (> 2 days) in cases of minor bleeding (other than gastrointestinal)
- the last efficacy rating of the bleeding episode was 'moderate' or 'none'

BEs treated with WILATE are summarized for all subjects (n=45) and subjects aged 5–16 years (n=11) in Table 14 . Among the 70 VWD subjects administered WILATE in clinical studies (excluding the PK study), 45 received on demand treatment for 1068 BEs. Using the above objective criteria, corresponding efficacy for each bleeding event was rated as being successful in 84% of the episodes. In these 45 subjects with BEs, 93% of the successfully treated BEs occurred in VWD type 3 subjects (n=25). In 11 pediatric subjects aged 5–16 years, efficacy was rated as being successful in 87.6% of BEs.

Table 14 Proportion of Successful Treatments of Bleeding Episodes with WILATE

 | Number of BEs* | Number of successfully treated BEs | % Successes (95% CI)
All subjects (n=45) | 1068 | 898 | 84.1 (81.8-86.2)
Subjects 5–16 years (n=11) | 234 | 205 | 87.6 (82.7-91.5)

*A “bleeding episode” may involve bleeding at multiple sites in this analysis.

Dosing information for 972 successfully treated “bleeding episodes” (1423 infusions), and 211 successfully treated bleeding episodes (289 infusions) in subjects aged 5–16 years, for regional bleeding is summarized in Table 15 . For the purpose of assigning success/failure to regional bleeding that occurred at the same time, bleeding at different sites over the same time span was counted as separate BEs. Thus, the number of these “episodes” is different from that in the overall evaluation for success/failure of WILATE in the treatment of BEs in Table 14 . The majority of BEs were treated for 1-3 days. In subjects with GI bleeds, the duration for product use to control bleeding was longer (up to 7 days).

Table 15 Administered Dosages (VWF:RCo in IU/kg) in Bleeding Episodes* Successfully Treated with WILATE: Mean ± SD (Range)

*For the purpose of this analysis, bleeding at each site is counted as a separate “episode”.

**“Other” includes mostly muscle bleeds, hematuria, ecchymosis, hematoma and other miscellaneous sites of bleeding.

Prevention of Bleeding in Surgery (Perioperative Management)

A prospective, open-label, single-arm, uncontrolled, multi-center clinical study was conducted to investigate the safety and hemostatic efficacy of WILATE in 28 subjects (19 female and 9 male) who underwent 30 surgeries. Two female subjects underwent 2 surgeries each. Subjects ranged in age from 12 to 74 years (median = 36). Three subjects were between 12 and 17 years old and 4 were 65 years or older. Six subjects had type 1 VWD, 1 had type 2A, 1 type 2B, and 20 had type 3 VWD. One type 1 and one type 3 subject had 2 surgeries each.

Twenty-one surgeries were classified as major (e.g. orthopedic joint replacement, cesarean section and vaginal deliveries, laminectomy, tonsillectomy, appendectomy, 3 rd molar extractions) and 9 were classified as minor (e.g. menisectomy, teeth extractions other than 3 rd molars, septoplasty, biopsy). Seven surgeries (3 major, 4 minor) were performed in type 1 VWD subjects, 2 surgeries (1 major, 1 minor) were performed in type 2 (A/B) VWD subjects, and 21 surgeries (17 major, 4 minor) were performed in type 3 VWD subjects. The types of surgery for the 9 minor procedures were: dental (n=5, 55.6%); orthopedic (n=2, 22.2%); ophthalmologic (n=1, 11.1%); and ear, nose and throat (n=1, 11.1%). The types of surgery for the 21 major procedures were: orthopedic (n=8, 38.1%); obstetric/gynecological (n=5, 23.8%); gastrointestinal (n=4, 19.0%); dental (n=2, 9.5%); and ear, nose and throat (n=2, 9.5%). The type of surgery according to VWD type were: VWD type 1 (n=7) – dental (n=4, 57.1%), orthopedic (n=2, 28.6%), and ear, nose and throat (n=1, 14.3%); VWD type 2 (A/B) (n=2) – orthopedic (n=1, 50%), and obstetric/gynecological (n=1, 50%); VWD type 3 (n=21) – orthopedic (n=7, 33.3%), gastrointestinal (n=4, 19.0%), obstetric/gynecological (n=4, 19.0%), dental (n=3, 14.3%), ear, nose and throat (n=2, 9.5%), and ophthalmologic (n=1, 4.8%).

Dosing was individualized based on in-vivo recovery results performed before surgery. Mean total loading dose per infusion was 51.4 IU/kg (median 52.1 IU/kg; range 27-77 IU/kg). Major surgeries required a mean loading dose of 54.7 IU/kg (median 55.5 IU/kg; range 36-69 IU/kg) in comparison with a mean loading dose of 41.9 IU/kg (median 37.5 IU/kg; range 27−77 IU/kg) for minor surgeries. Mean total maintenance dose per infusion was 28.5 IU/kg (median 28.5 IU/kg; range 8-63 IU/kg). Major surgeries required a mean maintenance infusion of 29.6 IU/kg (median 30 IU/kg; range 8-63 IU/kg) in comparison with a mean maintenance infusion of 21.6 IU/kg (median 20.6 IU/kg; range 14-38 IU/kg) for minor surgeries.

Efficacy of WILATE in surgical procedures was assessed by the surgeon at the conclusion of surgery and by the investigator-hematologist at 24 hours following completion of the final maintenance dose. Efficacy of WILATE was assessed using a stringent and objective 4-point ordinal efficacy scale (excellent, good, moderate, or none) based on estimated expected versus actual blood loss, transfusion requirements and post-operative bleeding and oozing. A rating of excellent or good was required to declare the outcome a success. An independent data monitoring committee (IDMC) additionally conducted an independent post hoc adjudication of intra- and post-operative assessments made by the surgeon/investigator-hematologist. In situations where the IDMC’s assessment differed from that of the surgeon and/or investigator-hematologist, the IDMC assessment took priority.

The overall efficacy of WILATE treatment for surgical procedures in this study was 96.7%. Treatment with WILATE was successful in all minor surgeries and in 95.2% of major surgeries (Table 16). It was also successful in all surgical procedures in VWD type 3 and type 2 subjects and in 85.7% of procedures in VWD type 1 subjects (Table 17). One failure was reported in a VWD type 1 subject undergoing lumbar laminectomy (major surgery) who experienced slightly greater blood loss (25 mL) than the expected maximum (20 mL).

Table 16 Hemostatic Efficacy Assessment by Severity of Surgery as Adjudicated by the IDMC (n=30)

 |  | Minor (n=9) |  |  | Major (n=21) |  |  | All surgeries (n=30)
Efficacy grade | n (%) | Rate | 98.75% CI | n (%) | Rate | 98.75% CI | n (%) | Rate | 98.75% CI
Success | 9 (100) | 1.000 | 0.569, 1.000 | 20 (95.2) | 0.952 | 0.704, 1.000 | 29 (96.7) | 0.967 | 0.784, 1.000
Failure | 0 |  |  | 1 (4.8) |  |  | 1 (3.3)

CI = confidence interval; IDMC = Independent Data Monitoring Committee; n = number of surgeries; rate = overall success rate.

Table 17 Hemostatic Efficacy Assessment by Type of VWD as Adjudicated by the IDMC (n=30)

 |  | VWD type 1 |  |  | VWD type 2 |  |  | VWD type 3
Efficacy grade | n (%) | Rate | 98.75% CI | n (%) | Rate | 98.75% CI | n (%) | Rate | 98.75% CI
Overall IDMC assessment
Success | 6 (85.7) | 0.857 | 0.328, 0.999 | 2 (100) | 1.000 | 0.079, 1.000 | 21 (100) | 1.000 | 0.785, 1.000
Failure | 1 (14.3) |  |  | 0 |  |  | 0

CI = confidence interval; IDMC = Independent Data Monitoring Committee; n = number of surgeries; rate = overall success rate; VWD = von Willebrand Disease.

In this study, actual blood loss (median) was lower than the expected maximal estimated blood loss in all types of surgeries. The actual blood loss was also lower than the average predicted blood loss in minor surgeries and equal in major surgeries (Table 18).

Table 18 Expected and Actual Estimated Blood Loss during Surgery

Estimated Blood Loss | Minor Surgery (n = 9) | Major Surgery (n= 21)
Expected Maximum - Median (range) mL | 50 (1-200) | 500 (20-2000)
Expected Average – Median (range) mL | 20 (1-100) | 100 (5-1500)
Actual - Median (range) mL | 15 (1-50) | 100 (0-1200)

Intra-operative transfusion was predicted in 5 subjects, but actually given in only 2. One subject received platelets intra-operatively for previously existing thrombocytopenia and one subject who underwent abdominal hysterectomy received one infusion of rejuvenated (in biochemical solution) packed red blood cells intra-operatively which was planned pre-surgery.

Three subjects received transfusions following surgery due to anemia and low hemoglobin values seen post-operatively.

Routine prophylaxis

A prospective, non-controlled, international, multi-center clinical study was conducted to demonstrate that WILATE is efficacious in bleeding prophylaxis in 33 evaluable subjects with VWD. The total annualized bleeding rates under prophylactic treatment in this study was compared to the annualized bleeding rates recorded for the same patients during a previous, non-interventional, on-demand treatment study. Annualized bleeding rates for all bleeding episodes, treated and untreated, for the on-demand treatment and the prophylaxis treatment are summarized in Table 19 .

Subjects ranged in age from 7 to 61 years (median = 18); 19 (57.6%) were male and 14 (42.4%) were female; 97% were white and 3% Black or African American . Nine subjects were between 6 and 11 years old, 6 were between 12 and 17 years old and 18 were 17 years or older. Six subjects had severe type 1 VWD, 5 had type 2A, and 22 had type 3 VWD. Subjects were treated for 12 months of prophylaxis with a dose of 20-40 IU/kg WILATE, mean dose = 30.57 IU/kg.

There were 10 (30.3%) subjects with 0 bleeding episodes and 15 (45.5%) subjects with 0 spontaneous bleeding episodes.

Table 19 Annualized Bleeding Rate in Adult Subjects and in Pediatric Subjects (6-17 Years Old) under Prophylaxis

 | on-demand treatment (n=33) | prophylaxis treatment (n=33) | Ratio of ABRs (95% confidence interval)
Annualized bleeding rate (± SD) per subject for all types of bleeds (excluding menstrual bleeds) | 33.38 ± 23.61 (median 24, range 11-114.5) | 5.24 ± 7.75 (median 2, range 0-35.8) | 0.16 (0.1,0.27)
Annualized bleeding rate (± SD) per subject - spontaneous bleeds | 24.42 ± 20.05 (median 19, range 4.9-92.8) | 3.23 ± 5.92 (median 1, range 0-24.6) | 0.14 (0.08, 0.25)
Annualized bleeding rate (± SD) per subject – joint bleeds | 7.56 ± 11.51 (median 3.43, range 0-39.1) | 0.53± 1.48 (median 0, range 0-6.9) | 0.08 (0.03, 0.18)

Hemophilia A

Routine prophylaxis

The efficacy of WILATE in routine prophylaxis was evaluated in a prospective, open-label, multicenter clinical study in which adults and adolescents aged 12-15 years were treated during 6 months of prophylaxis with 20-40 IU/kg WILATE, mean dose 32 IU/kg. Within the group of 55 subjects, of which 50 adults and 5 adolescents, there were 30 (54.6%) subjects with 0 bleeding episodes, 12 (21.8%) subjects with 1 bleeding episode, 4 (7.3%) subjects with 2 bleeding episodes, 4 (7.3%) subjects with 3 bleeding episodes, and 5 (9%) subjects with 5 or more bleeding episodes. Annualized bleeding rates for all bleeding episodes, treated and untreated, are summarized in Table 20 .

Table 20Annualized Bleeding Rate in Adult and Pediatric Subjects under Prophylaxis

 | Adults (n=50) | Adolescents (n=5)
Annualized bleeding rate (per subject) - spontaneous bleeds | 1.67 ± 3.11 (median 0, range 0-11.76) | 0 (median 0, range 0-0)
Annualized bleeding rate (per subject) for all types of bleeds | 2.39 ± 3.77 (median 0, range 0-15.69) | 0.4 ± 0.89 (median 0, range 0-2)

Treatment of bleeding episodes

The study presented above also provided data on the efficacy of WILATE in the treatment of bleeding episodes. The break-through bleeds were treated with WILATE doses adjusted to the severity of the bleed. Treatment efficacy was assessed by the patient or the patient’s parents (together with the investigator in case of on-site treatment) using the predefined criteria using an ordinal scale of excellent (abrupt pain relief and/or unequivocal improvement in objective signs of bleeding within approximately 8 hours after a single injection), good (definite pain relief and/or improvement in signs of bleeding within approximately 8–12 hours after an injection, requiring up to two injections for complete resolution), moderate (probable or slight beneficial effect within approximately 12 hours after the first injection, requiring more than two injections for complete resolution), or none (no improvement within 12 hours, or worsening of symptoms, requiring more than two injections for complete resolution).

In the per protocol population (n=52) of the study performed in adults and adolescents aged 12-15 years 57 bleeding episodes were treated with WILATE, of which 15 (26.3%) bleeding episodes were minor (e.g. early onset muscle and joint bleeds with no visible symptoms, such as little or no change in the range of motion of affected joint, mild restriction of mobility and activity, scrapes, superficial cuts, bruises, superficial mouth bleeds, and most nose bleeds), 32 (56.1%) were moderate (e.g. advanced soft tissue and muscle bleeds into the limbs, bleeding into the joint space, such as the elbow, knee, ankle, wrist, shoulder, hip, foot, or finger), 10 (17.5%) were major (e.g. complicated joint bleeds, bleeds of the pelvic muscles, eyes), and 0 (0%) were life-threatening (e.g. bleedings in the abdomen, digestive system or chest, central nervous system bleeds, bleedings in the area of the neck or throat or pharynx, or other major trauma). Forty-one bleeds (71.9%) were spontaneous and 16 (28.1%) were traumatic. Thirty-six bleeding episodes (63.2%) were managed with one WILATE injection, 12 (21.1%) were managed with two injections, 7 (12.3%) were managed with 3 injections, and 2 (3.6%) required more than 3 injections. The mean dose of WILATE per injection was 34 IU/kg. Treatment efficacy was judged as excellent for 16 (28.1%) bleeding episodes, good for 32 (56.1%) bleeding episodes and moderate for 9 (15.8%) bleeding episodes. Therefore, 84.2% of all bleeding episodes were treated successfully. The one bleeding episode in one subject younger than 16 years (bleeding in finger) was treated with a single injection of 62.81 IU/kg of WILATE with excellent efficacy (successful treatment).

Further efficacy data in the treatment of bleeding episodes is available from a pooled analysis of 37 subjects with hemophilia A included in 3 additional clinical studies. These subjects had at least 150 exposure days at the time of enrollment into the study and had been treated for at least 50 exposure days and 6 months in the study. The analysis encompassed 973 bleeding episodes, of which 924 (95%) were treated successfully.

15 REFERENCES

1. Mannucci P.M.: Venous thromboembolism in von Willebrand disease. Thromb Haemost 2002;88:378-379
2. Nichols WL, Hultin MB, et al. von Willebrand Disease (VWD): evidence-based diagnosis and management guidelines, the National Heart, Lung, and Blood Institute (NHLBI) Expert Panel report (USA). Haemophilia 2008; 14: 171-232
3. Mollison.P.L., Engelfriet C.P., Contreras M.: Some unfavourable effects of transfusion; in Klein H.G., Anstee D.J. (eds): Mollison's Blood Transfusion in Clinical Medicine. Blackwell Publishing, 2005, pp 666-700
4. Mannucci P.M., Federici A.B.: Antibodies to von Willebrand factor in von Willebrand disease; in Aledort L.M. (ed): Inhibitors to Coagulation Factors. New York, Plenum Press, 1995, pp 87-92
5. Kasper, C.K., Kipnis, S.A. Hepatitis and Clotting Factor Concentrates. JAMA 1972; 221:510
6. Biggs, R. Jaundice and Antibodies Directed Against Factors VIII and IX in Patients Treated for Haemophilia or Christmas Disease in the United Kingdom. Br J Haematol 1974; 26:313-329
7. Azzi A., Morfini M., Mannucci P.M.: The transfusion-associated transmission of parvovirus B19. Transfus.Med.Rev. 1999;13:194-204
8. Stadler M., et al. Characterisation of a novel high-purity, double virus inactivated von Willebrand Factor and Factor VIII concentrate (Wilate). Biologicals 2006; 34:281-288
9. Mannucci P.M.: Treatment of von Willebrand's disease. New England Journal of Medicine 2004;351:683-694

16 HOW SUPPLIED/STORAGE AND HANDLING

How Supplied

- WILATE is supplied in packages comprising of a single-dose vial of powder and a vial of diluent (Water for Injection with 0.1% Polysorbate 80), together with a Nextaro ® transfer device, a 10-mL syringe, an infusion set and two alcohol swabs.

Kit NDC Number | Size | Protein Amount
68982-182-01 68982-182-02 | 500 IU VWF:RCo and 500 IU FVIII activities in 5 mL 1000 IU VWF:RCo and 1000 IU FVIII activities in 10 mL | ≤ 7.5 mg ≤ 15.0 mg

- Each vial of WILATE contains the labeled amount of IU of VWF:RCo activity as measured using a manual agglutination method, and IU of FVIII activity measured with a chromogenic substrate assay.
- Components used in the packaging of WILATE are not made with natural rubber latex.

Storage and Handing

- Store WILATE for up to 36 months at +2°C to +8°C (36°F to 46°F) in the original containers to protect from light from the date of manufacture. Within this period, WILATE may be stored for a period of up to 6 months at room temperature (maximum of +25°C or 77°F). The starting date of room temperature storage should be clearly recorded on the product carton. Once stored at room temperature, the product must not be returned to the refrigerator. The shelf-life then expires after the storage at room temperature, or the expiration date on the product vial, whichever is earliest. Do not freeze.
- Do not use after the expiration date.
- Reconstitute the WILATE powder only directly before injection. Use the solution within 4 hours after reconstitution and discard any remaining solution.

17 PATIENT COUNSELING INFORMATION

- Advise the patients to read the FDA-approved patient labeling (Patient Information and Instructions for Use).
- Inform patients of the early signs of hypersensitivity reactions including hives, generalized urticaria, tightness of the chest, wheezing, hypotension, and anaphylaxis. If allergic symptoms occur, advise patients to discontinue the administration immediately and contact their physician to administer appropriate emergency treatment [ see Warnings and Precautions (5.1) ].
- Inform patients that undergoing multiple treatments with WILATE may increase the risk of thrombotic events thereby requiring frequent monitoring of plasma VWF:RCo and FVIII activities. [ see Warnings and Precautions (5.2) ].
- Inform patients that there is a potential of developing inhibitors to VWF and to FVIII, leading to an inadequate clinical response. Thus, if the expected VWF and to FVIII activity plasma levels are not attained, or if bleeding is not controlled with an adequate dose or repeated dosing, contact the treating physician.[ 3 ] [ see Warnings and Precautions (5.3) ].
- Inform patients that despite procedures for screening donors and plasma as well as those for inactivation or removal of infectious agents, the possibility of transmitting infective agents with plasma-derived products cannot be totally excluded [ see Warnings and Precautions (5.4) ].

Manufactured by:

Octapharma Pharmazeutika Produktionsges.m.b.H.

Oberlaaer Strasse 235

A-1100 Vienna, Austria

U.S. License No. 1646

Distributed by:

Octapharma USA Inc.

117 West Century Road

Paramus, NJ 07652

18 PATIENT PACKAGE INSERT

FDA-Approved Patient Labeling

Patient Information

WILATE

von Willebrand Factor/Coagulation Factor VIII Complex (Human)

Please read this Patient Information carefully before using WILATE and each time you get a refill, as there may be new information. This Patient Information does not take the place of talking with your healthcare provider about your medical condition or your treatment.

What is WILATE ?

WILATE is an injectable medicine that is used to treat and control bleeding in children and adults with vWD. It is also used for routine prophylaxis to reduce the number of bleeding episodes as well as for perioperative management of bleeding.

WILATE is used to treat and control bleeding in adolescents and adults with hemophilia A.

It is also used for routine prophylaxis to reduce the number of bleeding episodes.

Who should not use WILATE ?

You should not use WILATE if you are allergic to von Willebrand Factor or Factor VIII or any of the other ingredients of WILATE.

What should I tell my healthcare provider before using WILATE ?

Talk to your healthcare provider about any medical conditions that you have or have had.

Tell your healthcare provider about all of the prescription and non-prescription medicines you take, including over-the-counter medicines, dietary supplements, or herbal medicines.

Tell your healthcare provider if you are pregnant or nursing because WILATE might not be right for you.

How should I use WILATE ?

You get WILATE as an infusion into your vein after reconstitution of the lyophilized powder by mixing it with the supplied 5 or 10 milliliter sterile solvent (Water for Injection with 0.1% Polysorbate) with the supplied transfer device (see instruction for reconstitution and injection of WILATE).

Your healthcare provider will instruct you on how to do reconstitutions and infusions using sterile technique on your own or with the help of a family member, and they may watch you give yourself the first dose of WILATE.

You must carefully follow your healthcare provider’s instructions regarding the dose and schedule for infusing WILATE so that your treatment will work the best that it can for you.

WILATE comes in different dosage strengths. The actual number of international units (IU) of von Willebrand Factor and Factor VIII in the vial will be imprinted on the label and box. Always check the actual dosage strength printed on the label to make sure you are using the strength prescribed by your healthcare provider.

Contact your healthcare provider right away if bleeding is not controlled after using WILATE.

Talk to your healthcare provider before travelling. Plan to bring enough WILATE for your treatment during this time.

If you forget to use WILATE, do not inject a double dose to make up for the forgotten dose. Proceed with the next infusion as scheduled.

Do not stop using WILATE without consulting with your healthcare provider.

What are the possible side-effects of WILATE ?

Allergic reactions may occur. Call your healthcare provider or emergency department right away if you have any of the following symptoms: difficulty breathing, chest tightness, swelling of the face, rash or hives.

Because it is made from human blood, there is the risk that WILATE can potentially transmit disease or cause allergic reactions. Tell your healthcare provider if you have low-grade fever, rash, joint pain, nausea, vomiting, feeling tired, and yellowing of the skin.

Common side effects of WILATE in VWD are hypersensitivity reactions urticaria, chest discomfort, and dizziness.

A common side effect of WILATE in hemophilia A is fever.

These are not all of the possible side effects from WILATE. Ask your healthcare provider for more information. You are encouraged to report side effects to Octapharma USA Inc. at 1-866-766-4860 or FDA at 1-800-FDA-1088.

Talk to your healthcare provider about any side-effect that bothers you or that does not go away.

How should I store WILATE ?

Keep WILATE in its original box to protect it from exposure to light. Do not freeze WILATE .

You can store WILATE for up to 36 months at +2°C to +8°C (36°F to 46°F) from date of manufacture. Within this period, WILATE may be stored for a period of up to 6 months at room temperature (maximum of +25°C or 77°F). Note on the carton the date which the product was removed from the refrigerator.

After storage at room temperature, the product must be used or discarded, and it must not be put back into the refrigerator.

Do not use WILATE after the expiration date printed on the vial.

Do not use WILATE if the reconstituted solution is cloudy, contains particles, or is not colorless.

Use WILATE within 4 hours after mixing.

Dispose all materials, including any unused WILATE , in an appropriate container.

What else should I know about WILATE ?

Do not use WILATE for a medical condition for which it was not prescribed. Do not share WILATE with other people, even if they have the same diagnosis and symptoms that you have.

Resources at Octapharma available to patients

For more product information on WILATE, please visit www.wilateusa.com

For more information on patient assistance programs that are available to you, please contact the Octapharma Patient Support Center at 1-800-554-4440.

Manufactured by

Octapharma Pharmazeutika Produktionsges.m.b.H., Oberlaaer Strasse 235, A-1100 Vienna, Austria

U.S. License No. 1646

Distributed by

Octapharma USA, Inc., 117 West Century Road, Paramus, NJ 07652

wilate® is a registered trademark of Octapharma.

This Patient Information has been approved by the U.S. Food and Drug Administration.

Revised: March 2024

19 INSTRUCTIONS FOR USE

WILATE

von Willebrand Factor/Coagulation Factor VIII Complex (Human)

WILATE is supplied as a powder. Before it can be infused in your vein (intravenous injection), you must mix the powder with the supplied liquid diluent.

Do not attempt to do an infusion to yourself unless you have been taught how by your healthcare provider or hemophilia center.

Always follow the specific instructions given by your healthcare provider. The steps listed below are general guidelines for using WILATE. If you are unsure of the procedures, please call you healthcare provider before using WILATE. Your healthcare provider will prescribe the dose that you should take.

Preparation and Reconstitution

- WILATE is provided with a Nextaro ® transfer device for reconstitution of the WILATE powder in diluent.
- Reconstitute the powder only directly before injection.
- Because WILATE contains no preservatives, use the solution within 4 hours after reconstitution.

1) Warm the WILATE and diluent vials in the closed vials up to room temperature. If a water bath is used for warming, avoid water contact with the rubber stoppers or the caps of the vials. The temperature of the water bath should not exceed +37°C (98°F).
2) Remove the caps from the WILATE vial and the diluent vial and clean the rubber stoppers with an alcohol swab.

3) Open the transfer device package by peeling off the lid.. To maintain sterility, leave the Nextaro ® device in the clear outer packaging. The transfer device must be attached to the diluent vial first and then to the lyophilized powder vial. Otherwise, loss of vacuum occurs, and transfer of the diluent does not take place. If diluent is not completely transferred to the lyophilized powder vial during this process, contact Octapharma’s customer service.
Place the diluent vial on a level surface and hold the vial firmly. Ensure the Nextaro ® device remains in the outer packaging and invert the Nextaro ® device ensuring the blue part with the water droplets is on top of the diluent vial Push the Nextaro ® straight and firmly down until it snaps into place (Fig. 1). Do not twist while attaching. While holding onto the diluent vial, remove the outer package from the Nextaro ® , leaving the Nextaro ® attached firmly to the diluent vial (Fig. 2).

4) With the WILATE vial held firmly on a level surface, quickly invert the diluent vial with the Nextaro ® attached. Place the white part of the Nextaro ® on top of the WILATE vial and press down until it snaps into place (Fig. 3). Do not twist while attaching. The diluent will be drawn into the WILATE vial by the vacuum.
5) With both vials still attached, immediately start swirling the powder (WILATE) vial to ensure the powder is fully saturated. A slight whirlpool is formed by swirling. In order to avoid foaming, please do not shake the vial.

6) After 30 second, firmly hold both the white and blue parts of the Nextaro ® . Unscrew the Nextaro ® into two separate pieces (Fig. 4) and discard the empty diluent vial and the blue part of the Nextaro ® . Continue swirling until the powder in the WILATE vial has completely dissolved. This process may take several minutes.
The final solution is clear or slightly opalescent, colorless or slightly yellow. If the powder fails to dissolve completely or an aggregate is formed, do not use the preparation.

Administration

For intravenous use after reconstitution only.

1. Inspect final solution visually for particulate matter and discoloration prior to administration, whenever solution and container permit.
2. Do not mix WILATE with other medicinal products or administer simultaneously with other intravenous preparation in the same infusion set.
3. With the WILATE vial still upright, attach a plastic disposable syringe to the Nextaro ® (white plastic part). Invert the system and draw the reconstituted WILATE into the syringe.
4. Once WILATE has been transferred into the syringe, firmly hold the barrel of the syringe (keeping the syringe plunger facing down) and detach the Nextaro ® from the syringe. Discard the Nextaro ® (white plastic part) and empty WILATE vial.
5. Clean the intended injection site with an alcohol swab.
6. Attach a suitable infusion needle to the syringe.
7. Measure the patient’s pulse rate before and during the injection. If a marked increase in the pulse rate occurs, reduce the injection speed or interrupt the administration.
8. Inject the solution intravenously at a slow speed of 2-4 mL/minute.
9. Dispose unused product or waste material in accordance with local requirements.

For more product information on WILATE, please visit www.wilateusa.com

Manufactured by

Octapharma Pharmazeutika Produktionsges.m.b.H., Oberlaaer Strasse 235, A-1100 Vienna, Austria

U.S. License No. 1646

Distributed by

Octapharma USA, Inc., 117 West Century Road, Paramus, NJ 07652

wilate® is a registered trademark of Octapharma.

These Instructions for Use have been approved by the U.S. Food and Drug Administration

Revised: November 2024

20 PACKAGE LABEL - PRINCIPAL DISPLAY PANEL

von Willebrand Factor/Coagulation Factor VIII Complex (Human)

Octapharma Pharmazeutika Produktionsges.m.b.H

500IU/5mL

NDC 68982-182-01

1000IU/10mL

NDC 68982-182-02